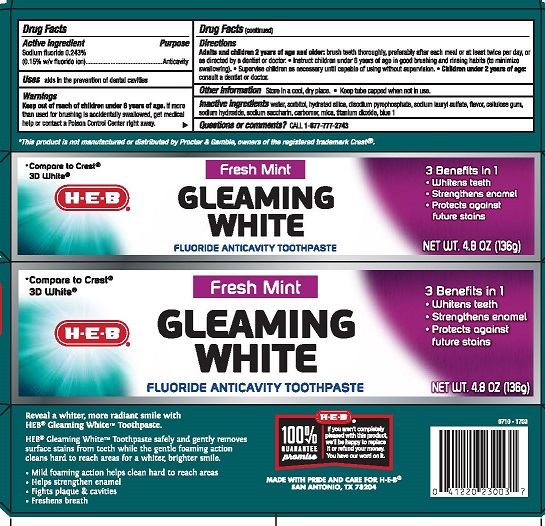 DRUG LABEL: HEB Gleaming White
NDC: 37808-330 | Form: PASTE, DENTIFRICE
Manufacturer: HEB
Category: otc | Type: HUMAN OTC DRUG LABEL
Date: 20250808

ACTIVE INGREDIENTS: SODIUM FLUORIDE 0.15 g/100 g
INACTIVE INGREDIENTS: SODIUM LAURYL SULFATE; SORBITOL; CARBOXYMETHYLCELLULOSE SODIUM, UNSPECIFIED FORM; SODIUM HYDROXIDE; SACCHARIN SODIUM; CARBOMER HOMOPOLYMER TYPE B (ALLYL PENTAERYTHRITOL OR ALLYL SUCROSE CROSSLINKED); TITANIUM DIOXIDE; FD&C BLUE NO. 1; WATER; HYDRATED SILICA; SODIUM ACID PYROPHOSPHATE; MICA

5820263 HEB Gleaming White Fresh Mint Anticavity Fluoride Toothpaste

Active ingredient

Sodium fluoride 0.243% (0.15% w/v fluoride ion)

Purpose

Anticavity

INDICATIONS AND USAGE

Usesaids in the prevention of dental cavities

Warnings

Keep out of reach of children under 6 years of age. If more than used for brushing is accidentally swallowed, get medical help or contact a Poison Control Center right away.

Directions

Adults and children 2 years of age and older: brush teeth thoroughly, preferably after each meal or at least twice per day, or as directed by a dentist or doctor.

- Instruct children under 6 years of age in good brushing and rinsing habits (to minimize swallowing).
- Supervise children as necessary until capable of using without supervision.
- Children under 2 years of age: consult a dentist or doctor.

Other information Store in a cool, dry place. · Keep tube capped when not in use.

INACTIVE INGREDIENT

Inactive ingredients water, sorbitol, hydrated silica, disodium pyrophosphate, sodium lauryl sulfate, flavor, cellulose gum, sodium hydroxide, sodium saccharin, carbomer, mica, titanium dioxide, blue 1

Questions or comments?CALL 1-877-777-2743

MADE WITH PRIDE AND CARE FOR H-E-B®

SAN ANTONIO, TX 78204

PACKAGE LABEL

HEB®

Fresh Mint

GLEAMING WHITE

FLUORIDE ANTICAVITY TOOTHPASTE

NET WT. 4.8 OZ (136g)